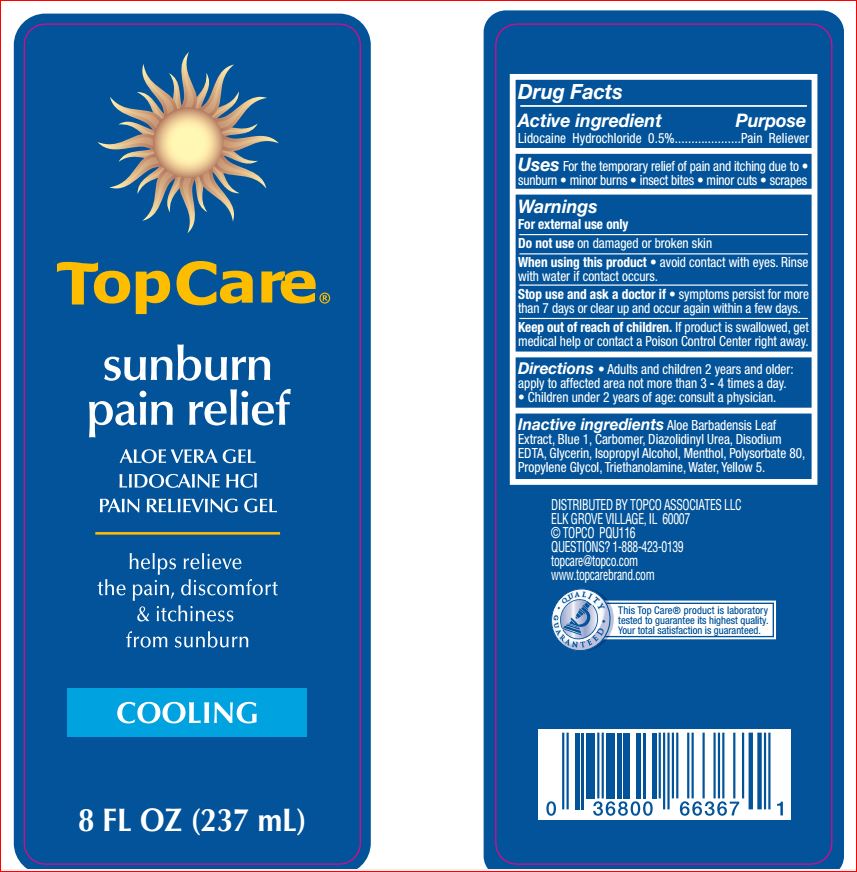 DRUG LABEL: Sunburn Pain relief
NDC: 36800-883 | Form: GEL
Manufacturer: Top Care
Category: otc | Type: HUMAN OTC DRUG LABEL
Date: 20180626

ACTIVE INGREDIENTS: LIDOCAINE HYDROCHLORIDE 0.5 g/100 mL
INACTIVE INGREDIENTS: ALOE VERA LEAF; CARBOMER HOMOPOLYMER TYPE C; Diazolidinyl Urea; EDETATE DISODIUM; Glycerin; Isopropyl Alcohol; Menthol; Polysorbate 80; Propylene Glycol; TROLAMINE; Water; FD&C YELLOW NO. 5

Drug Facts

Active ingredient Purpose

Lidocaine Hydrochloride 0.5% External analgesic

Uses for temporary relief of pain and itching due to

- sunburn
- minor burns
- insect bites
- cuts
- scrapes

Warnings

For external use only

When using this product

- avoid contact with eyes. Rinse with water if contact occurs.

Stop use and ask a doctor if

• symptoms last more than 7 days.

Directions

• adults and children 2 years of age and older: apply to affected area, not more than 3 to 4 times a day
• children under 2 years of age: consult a physician

Inactive ingredients

Aloe Barbadensis Leaf Juice, Blue 1, Carbomer, Diazolidinyl Urea, Disodium EDTA, Glycerin, Isopropyl Alcohol, Menthol, Polysorbate 80,
Propylene Glycol, Triethanolamine, Water, Yellow 5